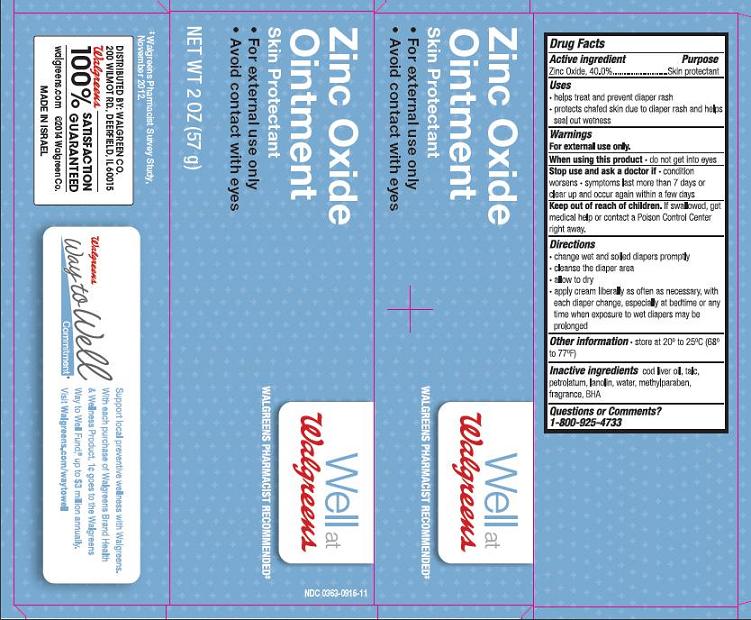 DRUG LABEL: Maximum Strength Diaper Rash
NDC: 0363-9160 | Form: CREAM
Manufacturer: Walgreen Company
Category: otc | Type: HUMAN OTC DRUG LABEL
Date: 20140904

ACTIVE INGREDIENTS: ZINC OXIDE 40 g/100 g
INACTIVE INGREDIENTS: COD LIVER OIL; TALC; PETROLATUM; LANOLIN; WATER; METHYLPARABEN; BUTYLATED HYDROXYANISOLE

Well at Walgreens Zinc Oxide Ointment

Active ingredient

Zinc Oxide, 40.0%

Purpose

Skin protectant

Uses

- helps treat and prevent diaper rash
- protects chafed skin due to diaper rash and helps seal out wetness

Warnings

For external use only.

When using this product

- do not get into eyes

Stop use and ask a doctor if

- condition worsens
- symptoms last more than 7 days or clear up and occur again within a few days

Keep out of reach of children.

If swallowed, get medical help or contact a Poison Control Center right away.

Directions

- change wet and soiled diapers promptly
- cleanse the diaper area
- allow to dry
- apply cream liberally as often as necessary, with each diaper change, especially at bedtime or any time when exposure to wet diapers may be prolonged

Other information

store at 20° to 25°C (68° to 77°F)

Inactive ingredients

cod liver oil, talc, petrolatum, lanolin, water, methylparaben, fragrance, BHA

Questions or Comments?

1-800-925-4733

Package/Label Principal Display Panel

Well at Walgreens Zinc Oxide Ointment

Skin Protectant

- For external use only
- Avoid contact with eyes

NET WT 2 OZ (57 g)

Walgreens Pharmacist Recommended‡

‡Walgreens Pharmacist Survey Study, November 2012.

Walgreens Way to Well Commitment®
Support local preventive wellness with Walgreens.
With each purchase of Walgreens Brand Health & Wellness Product, 1¢ goes to Walgreens Way to Well Fund, up to $3 million annually.
Visit Walgreens.com/waytowell

DISTRIBUTED BY:
WALGREEN CO.
200 WILMOT RD., DEERFIELD, IL 60015
100% SATISFACTION GUARANTEED
walgreens.com © 2014 Walgreen Co.
MADE IN ISRAEL

Container Label